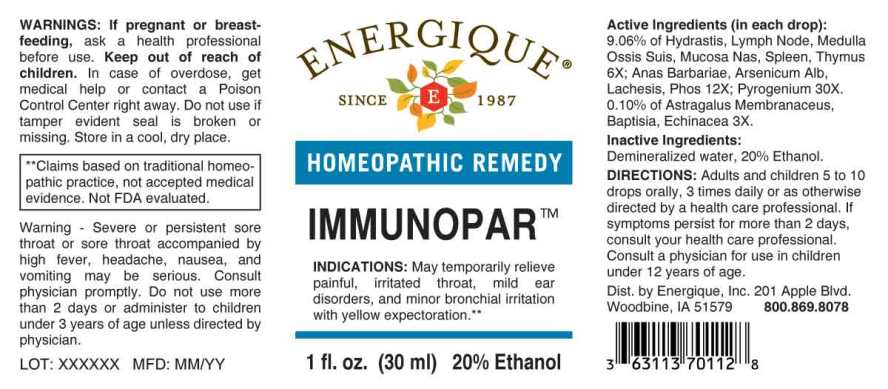 DRUG LABEL: IMMUNOPAR
NDC: 44911-0636 | Form: LIQUID
Manufacturer: Energique, Inc.
Category: homeopathic | Type: HUMAN OTC DRUG LABEL
Date: 20241028

ACTIVE INGREDIENTS: ASTRAGALUS PROPINQUUS ROOT 3 [hp_X]/1 mL; BAPTISIA TINCTORIA ROOT 3 [hp_X]/1 mL; ECHINACEA ANGUSTIFOLIA WHOLE 3 [hp_X]/1 mL; GOLDENSEAL 6 [hp_X]/1 mL; SUS SCROFA LYMPH 6 [hp_X]/1 mL; SUS SCROFA BONE MARROW 6 [hp_X]/1 mL; SUS SCROFA NASAL MUCOSA 6 [hp_X]/1 mL; SUS SCROFA SPLEEN 6 [hp_X]/1 mL; SUS SCROFA THYMUS 6 [hp_X]/1 mL; CAIRINA MOSCHATA HEART/LIVER AUTOLYSATE 12 [hp_X]/1 mL; ARSENIC TRIOXIDE 12 [hp_X]/1 mL; LACHESIS MUTA VENOM 12 [hp_X]/1 mL; PHOSPHORUS 12 [hp_X]/1 mL; RANCID BEEF 30 [hp_X]/1 mL
INACTIVE INGREDIENTS: WATER; ALCOHOL

DRUG FACTS:

ACTIVE INGREDIENTS:

(in each drop): 9.06% of Hydrastis Canadensis 6X, Lymph Node (SUIS) 6X, Medulla Ossis Suis 6X, Mucosa Nasalis Suis 6X, Spleen (Suis) 6X, Thymus (Suis) 6X, Anas Barbariae,Hepatis ET Cordis Extractum 12X, Arsenicum Album 12X, Lachesis Mutus12X, Phosphorus 12X, Pyrogenium 30X, 0.10% of Astragalus Membranaceus12X, Baptisia Tinctoria 3X, Echinacea (Angustifolia) 3X

INDICATIONS:

May temporarily relieve Painful, irrated throat, mild ear disorders, and minor bronchial irritation with yellow expectoration.**

**Claims based on traditional homeopathic practice, not accepted medical evidence. Not FDA evaluated.

WARNINGS:

If pregnant or breast-feeding, ask a health professional before use.

Keep out of reach of children. In case of overdose, get medical help or contact a Poison Control Center right away.

Do not use if tamper evident seal is broken or missing. Store in a cool, dry place.

DIRECTIONS:

Adults and children 5 to 10 drops orally, 3 times daily or as otherwise directed by a health care professional. If symptoms persist for more than 2 days, consult your health care professional. Consult a physician for use in children under 12 years of age.

INACTIVE INGREDIENTS:

Demineralized water, 20% Ethanol.

Keep out of reach of children. In case of overdose, get medical help or contact a Poison Control Center right away.

INDICATIONS:

May temporarily relieve Painful, irrated throat, mild ear disorders, and minor bronchial irritation with yellow expectoration.**

**Claims based on traditional homeopathic practice, not accepted medical evidence. Not FDA evaluated.

QUESTIONS:

Dist. by Energique, Inc.

201 Apple Blvd

Woodbine, IA 51579

800-869-8078

PACKAGE LABEL DISPLAY:

ENERGIQUE

SINCE 1987

HOMEOPATHIC REMEDY

IMMUNOPAR

1 fl. oz. (30 ml)